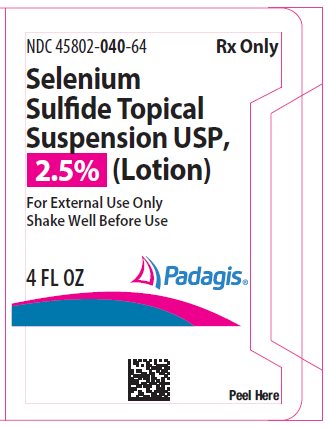 DRUG LABEL: SELENIUM SULFIDE
NDC: 45802-040 | Form: LOTION
Manufacturer: Padagis Israel Pharmaceuticals Ltd
Category: prescription | Type: HUMAN PRESCRIPTION DRUG LABEL
Date: 20250531

ACTIVE INGREDIENTS: SELENIUM SULFIDE 2.5 mg/100 mL
INACTIVE INGREDIENTS: BENTONITE; CITRIC ACID MONOHYDRATE; GLYCOL STEARATE; LAURIC DIETHANOLAMIDE; SODIUM LAURYL SULFATE; SODIUM PHOSPHATE, MONOBASIC, UNSPECIFIED FORM; TITANIUM DIOXIDE; WATER

Selenium Sulfide Topical Suspension USP, 2.5% (Lotion)

For External Use Only

Shake Well Before Use

Rx Only

APPLICATION INSTRUCTIONS

Keep tightly capped. SHAKE WELL BEFORE USING.

Product may damage jewelry; remove jewelry before use.

For treatment of dandruff and seborrheic dermatitis of the scalp:

1. Massage about 1 or 2 teaspoonsful of suspension into wet scalp.

2. Allow to remain on scalp for 2 to 3 minutes.

3. Rinse scalp thoroughly.

4. Repeat application and rinse thoroughly.

5. After treatment, wash hands well.

6. Repeat treatments as directed by physician.

For treatment of tinea versicolor:

1. Apply to affected areas and lather with a small amount of water.

2. Allow to remain on skin for 10 minutes.

3. Rinse body thoroughly.

4. Repeat this procedure once a day for seven days.

DESCRIPTION

A liquid antiseborrheic, antifungal preparation for topical application. Selenium sulfide has the molecular formula SeS2 and has a molecular weight of 143.09.

CONTAINS:

Selenium sulfide 2.5%; bentonite, citric acid, cocoamphocarboxyglycinate, ethylene glycol monostearate, fragrance, glycerol monoricinoleate, lauramide DEA, sodium lauryl sulfate, sodium phosphate (monobasic), titanium dioxide, and water.

CLINICAL PHARMACOLOGY

Selenium sulfide appears to have a cytostatic effect on cells of the epidermis and follicular epithelium, thus reducing corneocyte production.

INDICATIONS AND USAGE

For the treatment of tinea versicolor, seborrheic dermatitis of the scalp, and dandruff.

CONTRAINDICATIONS

This product should not be used by patients allergic to any of its components.

PRECAUTIONS

General -

Should not be used when acute inflammation or exudation is present as increased absorption may occur.

Information for Patients -

Application to skin or scalp may produce skin irritation or sensitization. If sensitivity reactions occur, use should be discontinued. May be irritating to mucous membranes of the eyes and contact with this area should be avoided. When applied to the body for treatment of tinea versicolor, Selenium Sulfide Topical Suspension USP, 2.5% (Lotion) may produce skin irritation especially in the genital area and where skin folds occur. These areas should be thoroughly rinsed after application.

Carcinogenesis -

Studies in mice using dermal application of 25% and 50% solutions of 2.5% selenium sulfide topical suspension, over an 88 week period, indicated no carcinogenic effects.

Pregnancy -

WHEN USED ON BODY SURFACES FOR THE TREATMENT OF TINEA VERSICOLOR, SELENIUM SULFIDE IS CLASSIFIED AS PREGNANCY CATEGORY "C". Animal reproduction studies have not been conducted with Selenium Sulfide Topical Suspension USP, 2.5% (Lotion). It is also not known whether Selenium Sulfide Topical Suspension USP, 2.5% (Lotion) can cause fetal harm when applied to body surfaces of a pregnant woman or can affect reproduction capacity. Under ordinary circumstances Selenium Sulfide Topical Suspension USP, 2.5% (Lotion) should not be used for the treatment of tinea versicolor in pregnant women.

Pediatric Use -

Safety and effectiveness in infants have not been established.

ADVERSE REACTIONS

In decreasing order of severity: skin irritation, occasional reports of increase in amount of normal hair loss, discoloration of hair (can be avoided or minimized by thorough rinsing of hair after treatment). As with other shampoos, oiliness or dryness of hair and scalp may occur.

OVERDOSAGE

Accidental Oral Ingestion-

Selenium Sulfide Topical Suspension USP, 2.5% (Lotion) is intended for external use only. There have been no documented reports of serious toxicity in humans resulting from acute ingestion of Selenium Sulfide Topical Suspension USP, 2.5% (Lotion); however, acute toxicity studies in animals suggest that ingestion of large amounts could result in potential human toxicity. For this reason, evacuation of the stomach contents should be considered in cases of acute oral ingestion.

DOSAGE AND ADMINISTRATION

See application instructions on rear panel of this bottle. For treatment of dandruff and seborrheic dermatitis: For the usual case, two applications each week for two weeks will afford control. After this, the suspension may be used at less frequent intervals - weekly, every two weeks, or even every 3 or 4 weeks in some cases. The preparation should not be applied more frequently than required to maintain control.

For treatment of tinea versicolor: Apply to affected areas and lather with a small amount of water. Allow product to remain on skin for 10 minutes, then rinse the body thoroughly. Repeat this procedure once a day for seven days.

HOW SUPPLIED

Selenium Sulfide Topical Suspension USP, 2.5% (Lotion) is available as follows:

4 fl oz plastic bottle (NDC 45802-040-64).

WARNINGS AND PRECAUTIONS:

For External Use Only. Do not use on broken skin or inflamed areas. If allergic reactions occur, discontinue use. Avoid getting shampoo in eyes or in contact with genital area as it may cause irritation and burning.

KEEP THIS AND ALL MEDICATIONS OUT OF REACH OF CHILDREN.

STORAGE AND HANDLING

Store at 20°-25°C (68°-77°F) [see USP Controlled Room Temperature].

Manufactured by Padagis, Minneapolis, MN 55427

www.padagis.com

Rev 05-25

27G26 RC F2/27G26 RC B2

Principal Display Panel

NDC 45802-040-64

Rx Only

Selenium Sulfide Topical Suspension USP, 2.5% (Lotion)

For External Use Only

Shake Well Before Use

4 FL OZ

Peel Here